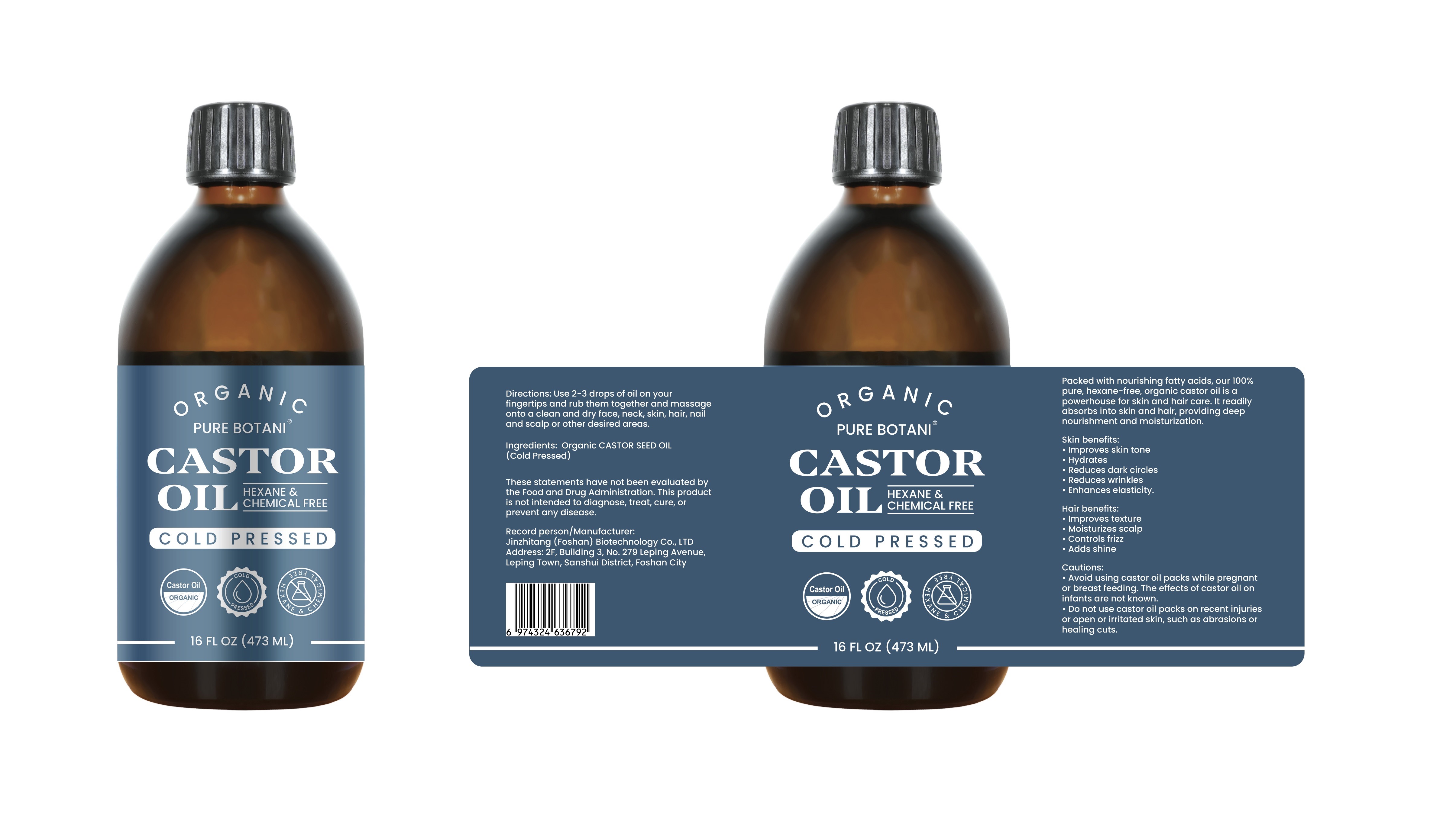 DRUG LABEL: Organic Castor Oil
NDC: 87104-0102 | Form: OIL
Manufacturer: Jinzhitang (Foshan) Biotechnology Co., Ltd.
Category: otc | Type: HUMAN OTC DRUG LABEL
Date: 20251029

ACTIVE INGREDIENTS: CASTOR OIL 473 g/473 mL

WARNINGS

Cautions:
Avoid using castor oil packs while pregnantor breast feeding. The effects of castor oil oninfants are not known.Do not use castor oil packs on recent injuriesor open or irritated skin, such as abrasions orhealing cuts.

DOSAGE AND ADMINISTRATION

Use 2-3 drops of oil on yourfingertips and rub them together and massageonto a clean and dry face, neck, skin, hair, nailand scalp or other desired areas.

INACTIVE INGREDIENT

1. none

INDICATIONS AND USAGE

1. Avoid using castor oil packs while pregnantor breast feeding. The effects of castor oil oninfants are not known.
2. Do not use castor oil packs on recent injuriesor open or irritated skin, such as abrasions orhealing cuts.

KEEP OUT OF REACH OF CHILDREN

1. Avoid using castor oil packs while pregnantor breast feeding. The effects of castor oil oninfants are not known.
2. KEEP OUT OF REACH OF CHILDREN SECTION

PURPOSE

Packed with nourishing fatty acids,our 100%pure, hexane-free, organic castor oil is apowerhouse for skin and hair care. lt readilyabsorbs into skin and hair, providing deepnourishment and moisturization.